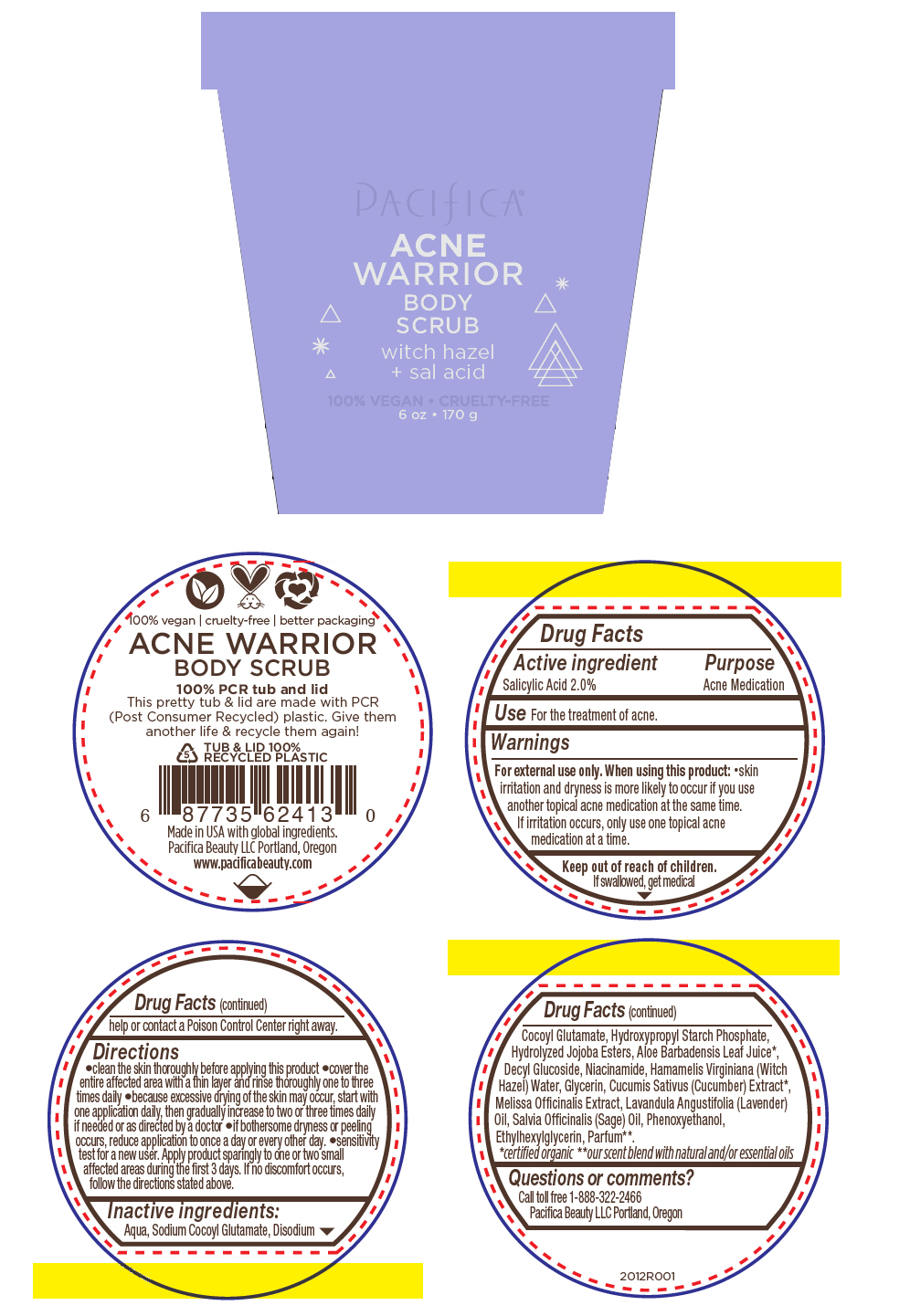 DRUG LABEL: PACIFICA ACNE WARRIOR BODY SCRUB
NDC: 61197-400 | Form: CREAM
Manufacturer: Pacifica Beauty LLC.
Category: otc | Type: HUMAN OTC DRUG LABEL
Date: 20210108

ACTIVE INGREDIENTS: Salicylic Acid 20 mg/1 g
INACTIVE INGREDIENTS: Water; Sodium Cocoyl Glutamate; Disodium Cocoyl Glutamate; Hydrolyzed Jojoba Esters (Acid Form); Aloe Vera Leaf; Decyl Glucoside; Niacinamide; Hamamelis Virginiana Top Water; Glycerin; Cucumber; Melissa Officinalis Whole; Lavender Oil; Sage Oil; Phenoxyethanol; Ethylhexylglycerin

PACIFICA® ACNE WARRIOR BODY SCRUB

Drug Facts

Active ingredient

Salicylic Acid 2.0%

Purpose

Acne Medication

Use

For the treatment of acne.

Warnings

For external use only.

When using this product

- skin irritation and dryness is more likely to occur if you use another topical acne medication at the same time. If irritation occurs, only use one topical acne medication at a time.

Keep out of reach of children.

If swallowed, get medical help or contact a Poison Control Center right away.

Directions

- clean the skin thoroughly before applying this product
- cover the entire affected area with a thin layer and rinse thoroughly one to three times daily
- because excessive drying of the skin may occur, start with one application daily, then gradually increase to two or three times daily if needed or as directed by a doctor
- if bothersome dryness or peeling occurs, reduce application to once a day or every other day.
- sensitivity test for a new user. Apply product sparingly to one or two small affected areas during the first 3 days. If no discomfort occurs, follow the directions stated above.

Inactive ingredients

Aqua, Sodium Cocoyl Glutamate, Disodium Cocoyl Glutamate, Hydroxypropyl Starch Phosphate, Hydrolyzed Jojoba Esters, Aloe Barbadensis Leaf Juice [certified organic] , Decyl Glucoside, Niacinamide, Hamamelis Virginiana (Witch Hazel) Water, Glycerin, Cucumis Sativus (Cucumber) Extract, Melissa Officinalis Extract, Lavandula Angustifolia (Lavender) Oil, Salvia Officinalis (Sage) Oil, Phenoxyethanol, Ethylhexylglycerin, Parfum [our scent blend with natural and/or essential oils] .

Questions or comments?

Call toll free 1-888-322-2466

Pacifica Beauty LLC Portland, Oregon

PRINCIPAL DISPLAY PANEL - 170 g Cup Label

PACIFICA®
ACNE
WARRIOR
BODY
SCRUB
witch hazel
+ sal acid

100% VEGAN • CRUELTY-FREE

6 oz • 170 g